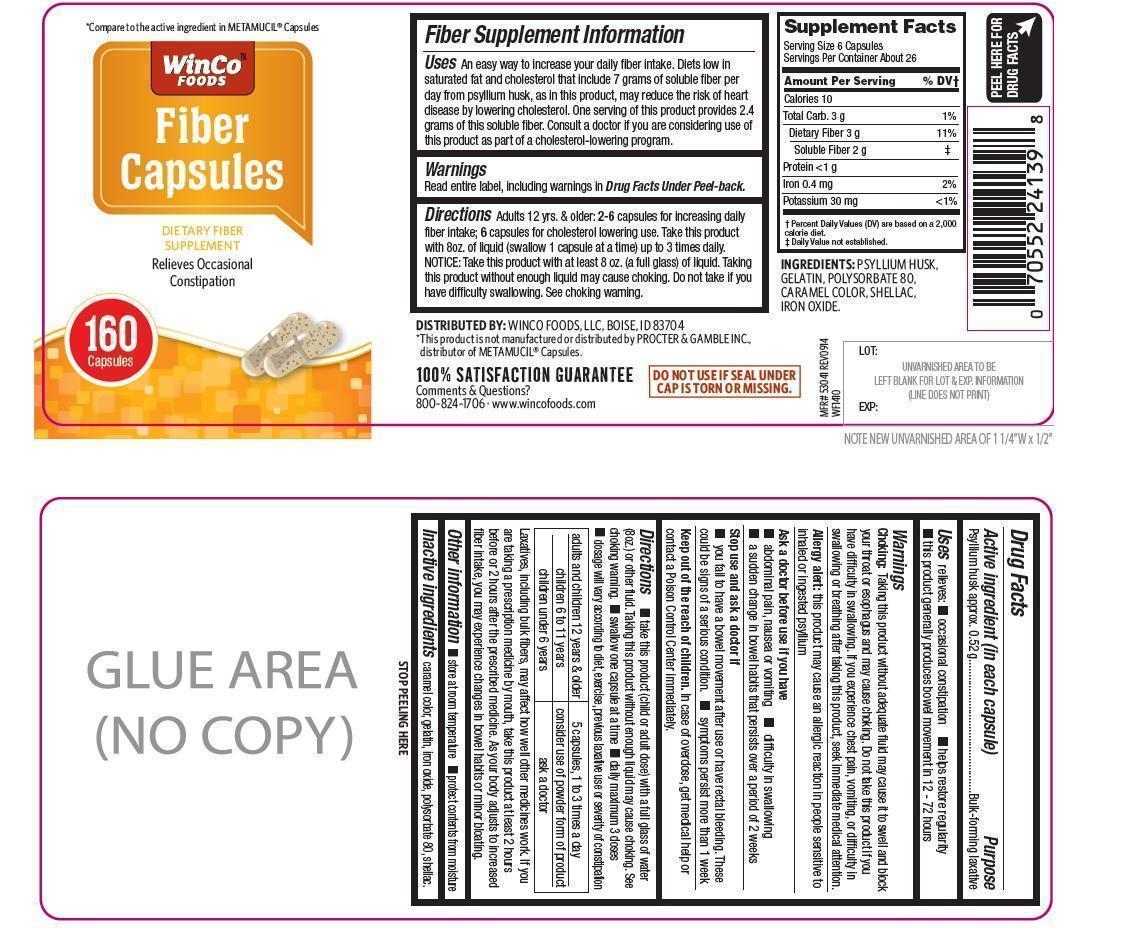 DRUG LABEL: Fiber
NDC: 67091-222 | Form: CAPSULE
Manufacturer: WinCo Foods, LLC
Category: otc | Type: HUMAN OTC DRUG LABEL
Date: 20141126

ACTIVE INGREDIENTS: PSYLLIUM HUSK 0.52 g/1 1
INACTIVE INGREDIENTS: CARAMEL; GELATIN; POLYSORBATE 80; SHELLAC; BROWN IRON OXIDE

Fiber Capsules

Active ingredient (in each capsule)

Psyllium husk approx. 0.52 g

Purpose

Bulk-forming laxative

Uses

relieves:

- occasional constipation
- helps restore regularity
- this product generally produces bowel movement in 12-72 hours

Warnings

Choking: Taking this product without adequate fluid may cause it to swell and block your throat or esophagus and may cause choking. Do not take this product if you have difficulty in swallowing. If you experience chest pain, vomiting, or difficulty in swallowing or breathing after taking this product, seek immediate medical attention.

Allergy alert: this product may cause an allergic reaction in people sensitive to inhaled or ingested psyllium

Ask a doctor before use if you have

- abdominal pain, nausea or vomiting
- difficulty in swallowing
- a sudden change in bowel habits that persists over a period of 2 weeks

Stop use and ask a doctor if

- you fail to have a bowel movement after use or have rectal bleeding. These could be signs of a serious condition.
- symptoms persist more than 1 week

Keep out of reach of children. In case of overdose, get medical help or contact a Poison Control Center immediately

Directions

- take this product (child or adult dose) with a full glass of water (8oz.) or other fluid. Taking this product without enough liquid may cause choking. See choking warning.
- swallow one capsule at a time
- daily maximum 3 doses
- dosage will vary according to diet, exercise, previous laxative use or severity of constipation.

adults and children 12 years and older | 5 capsules, 1 to 3 times a day
children 6 to 11 years | consider use of powder form of product
children under 6 years | ask a doctor

Laxatives, including bulk fibers, may affect how well other medicines work. If you are taking a prescription medicine by mouth, take this product at least 2 hours before or 2 hours after the prescribed medicine. As your body adjusts to increased fiber intake, you may experience changes in bowel habits or minor bloating.

Other information

- store at room temperature
- protect contents from moisture.

Inactive ingredients

caramel color, gelatin, iron oxide, polysorbate 80, shellac

Fiber Supplement information

Uses: An easy way to increase your daily fiber intake. Diets low in saturated fat and cholesterol that include 7 grams of soluble fiber per day from psyllium husk, as in this product, may reduce the risk of heart disease by lowering cholesterol. One serving of this product provides 2.4 grams of this soluble fiber. consult a doctor if you are considering use of this product as part of a cholesterol lowering program.

Warnings: Read entire label, including warnings in Drug Facts under peel-back

Directions: Adults 12 years and older: 2-6 capsules for increasing daily fiber intake; 6 capsules for cholesterol lowering use. Take this product 8oz. of liquid (swallow 1 capsule at a time) up to 3 times daily. NOTICE: Take this product atleast 8 oz . (a full glass) of liquid. Taking this product without enough liquid may cause choking. Do not take if you have difficulty swallowing. See choking warning.

PDP

*Compare to the active ingredient in METAMUCIL® Capsules

Fiber Capsules

Dietary Fiber Supplement

Relieves Occasional Constipation

160 capsules